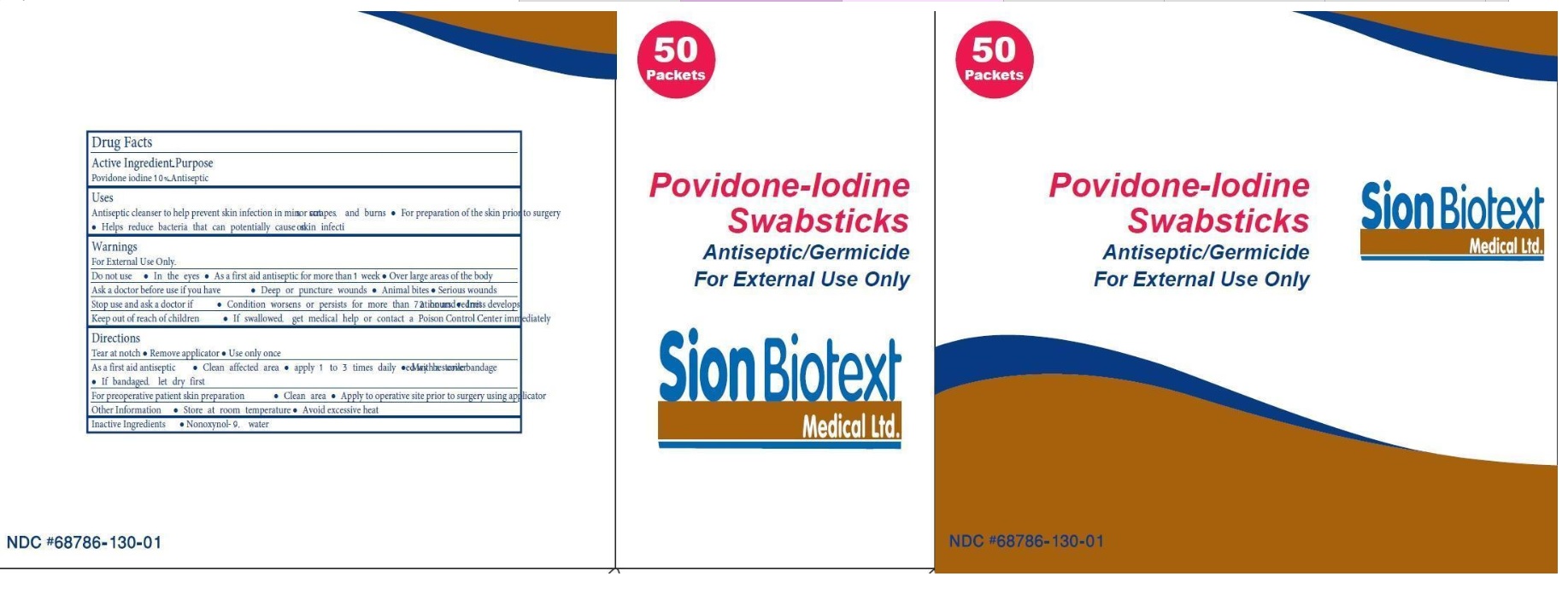 DRUG LABEL: Povidone Iodine
NDC: 68786-130 | Form: SWAB
Manufacturer: Sion Biotext Medical Ltd
Category: otc | Type: HUMAN OTC DRUG LABEL
Date: 20260112

ACTIVE INGREDIENTS: POVIDONE-IODINE 0.1 g/1 1
INACTIVE INGREDIENTS: NONOXYNOL-9; WATER

Povidone Iodine Prep Pad

Active Ingredient

Povidone Iodine 10%

Purpose

Antiseptic

Uses

- Antiseptic cleanser to help prevent infection in minor cuts, scrapes and burns.
- For preparation of the skin prior to surgery.
- Helps reduce bacteria that can potentially cause skin infection.

Warnings

For External Use Only.

Do not use

- In the eyes
- As a first aid antiseptic for more than 1 week
- Over large areas of the body

Ask a doctor before use if you have

- Deep or puncture wounds
- Animal bites
- Serious burns

Stop use and ask a doctor if

- Condition worsens or persists for more than 72 hours
- Irritation and redness develops

Keep out of reach of children

If swallowed, get medical help or contact a Poison Control Center right away.

Directions

- Tear at notch
- Remove applicator
- Use only once

As a first aid antispetic

- Clean affected area
- apply 1-3 times daily
- May be covered with a sterile bandage
- If bandaged, let dry first.

For preoperative patient skin preparation

- Clean area
- Apply to operative site prior to surgery using applicator

Other Information

- Store at room temperature
- Avoid excessive heat

Inactive Ingredients

Nonoxynol-9, water

Principal Display Panel

NDC 68786-130-01

50 Packets

Povidone-Iodine Swabsticks

Antispetic/Germicide

For External Use Only

Sion Biotext Medical Ltd.